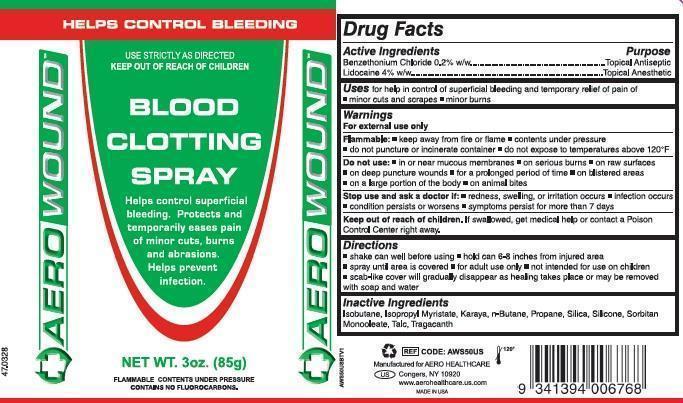 DRUG LABEL: Aerowound Blood Clotting First Aid
NDC: 55305-114 | Form: AEROSOL, SPRAY
Manufacturer: Aero Healthcare, LLC.
Category: otc | Type: HUMAN OTC DRUG LABEL
Date: 20140820

ACTIVE INGREDIENTS: LIDOCAINE 756.5 mg/85 g; BENZETHONIUM CHLORIDE 76.5 mg/85 g
INACTIVE INGREDIENTS: ISOBUTANE; ISOPROPYL MYRISTATE; KARAYA GUM; BUTANE; PROPANE; SILICON DIOXIDE; 3-(TRIETHOXYSILYL)PROPYLAMINE; SORBITAN MONOOLEATE; TALC; TRAGACANTH

AEROWOUND BLOOD CLOTTING SPRAY

Active Ingredients

Benzethonium Chloride 0.2% w/w
Lidocaine 4% w/w

Purpose

Topical Antiseptic
Topical Anesthetic

Uses

for help in control of superficial bleeding and temporary relief of pain of:

- minor cuts and scrapes
- minor burns

Warnings

For external use only

Flammable

- keep away from flame
- contents under pressure
- do not puncture or incinerate
- do not expose to temperatures above 120°F

Do not use

- in or near mucous membranes
- on serious burns
- on raw surfaces
- on deep puncture wounds
- for a prolonged period of time
- on blistered areas
- on a large portion of the body
- on animal bites

Stop use and ask doctor if

- redness, swelling, or irritation occurs
- infection occurs
- condition persists or worsens
- symptoms persist for more than 7 days

Keep out of reach of children.

If swallowed, get medical help or contact a Poison Control Center right away.

Directions

- shake can well before using
- hold 6-8 inches from moist injured area
- spray until area is covered
- for adult use only
- not intended for use on children
- scab-like cover will gradually disappear as healing takes place or may be removed with soap and water

Inactive Ingredients

Isobutane, Isopropyl Myristate, Karaya, n-Butane, Propane, Silica, Silicone, Sorbitan Monooleate, Talc, Tragacanth